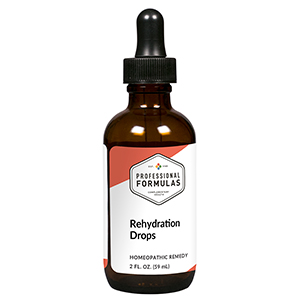 DRUG LABEL: Rehydration Drops
NDC: 63083-2175 | Form: LIQUID
Manufacturer: Professional Complementary Health Formulas
Category: homeopathic | Type: HUMAN OTC DRUG LABEL
Date: 20190815

ACTIVE INGREDIENTS: ARABICA COFFEE BEAN 1 [hp_X]/59 mL; TARAXACUM OFFICINALE 1 [hp_X]/59 mL; HYPERICUM PERFORATUM WHOLE 3 [hp_X]/59 mL; ADENOSINE TRIPHOSPHATE 4 [hp_X]/59 mL; SILICON DIOXIDE 4 [hp_X]/59 mL; SUS SCROFA ADRENAL GLAND 6 [hp_X]/59 mL; BOS TAURUS HYPOTHALAMUS 6 [hp_X]/59 mL; BEEF KIDNEY 6 [hp_X]/59 mL; .GAMMA.-AMINOBUTYRIC ACID 6 [hp_X]/59 mL; GERMANIUM 12 [hp_X]/59 mL; SEROTONIN 12 [hp_X]/59 mL
INACTIVE INGREDIENTS: ALCOHOL; WATER

C175

ACTIVE INGREDIENTS

Coffea cruda 1X
Taraxacum officinale 1X
Hypericum perforatum 3X, 6X, 12X
ATP 4X, 6X, 12X, 30X
Silicea 4X, 6X, 8X
Adrenal 6X, 12X
Hypothalamus 6X, 12X
Kidney 6X, 12X
GABA 6X, 12X, 30X
Germanium 12X
Serotonin 12X

QUESTIONS

Professional Formulas

PO Box 2034 Lake Oswego, OR 97035

INDICATIONS

For the temporary relief of occasional headache, dry mouth, dry skin, or increased thirst.*

PURPOSE

*Claims based on traditional homeopathic practice, not accepted medical evidence. Not FDA evaluated.

WARNINGS

In case of overdose, get medical help or contact a poison control center right away.

Keep out of the reach of children.

PREGNANCY OR BREAST FEEDING

If pregnant or breastfeeding, ask a healthcare professional before use.

DIRECTIONS

Place drops under tongue 30 minutes before/after meals. Adults and children 12 years and over: Take 10 drops up to 3 times per day for up to 6 weeks. For immediate onset of symptoms, take 10 to 15 drops every 15 minutes up to 3 hours. For less severe symptoms, take 10-15 drops hourly up to 8 hours. Consult a physician for use in children under 12 years of age.

OTHER INFORMATION

Tamper resistant. If seal is broken, do not use. After opening, close container tightly and store at room temperature away from heat.

INACTIVE INGREDIENTS

15% ethanol, purified water, 15% vegetable glycerin (from soy).

LABEL

Est 1985

Professional Formulas

Complementary Health

Rehydration Drops

Homeopathic Remedy

2 FL. OZ. (59 mL)